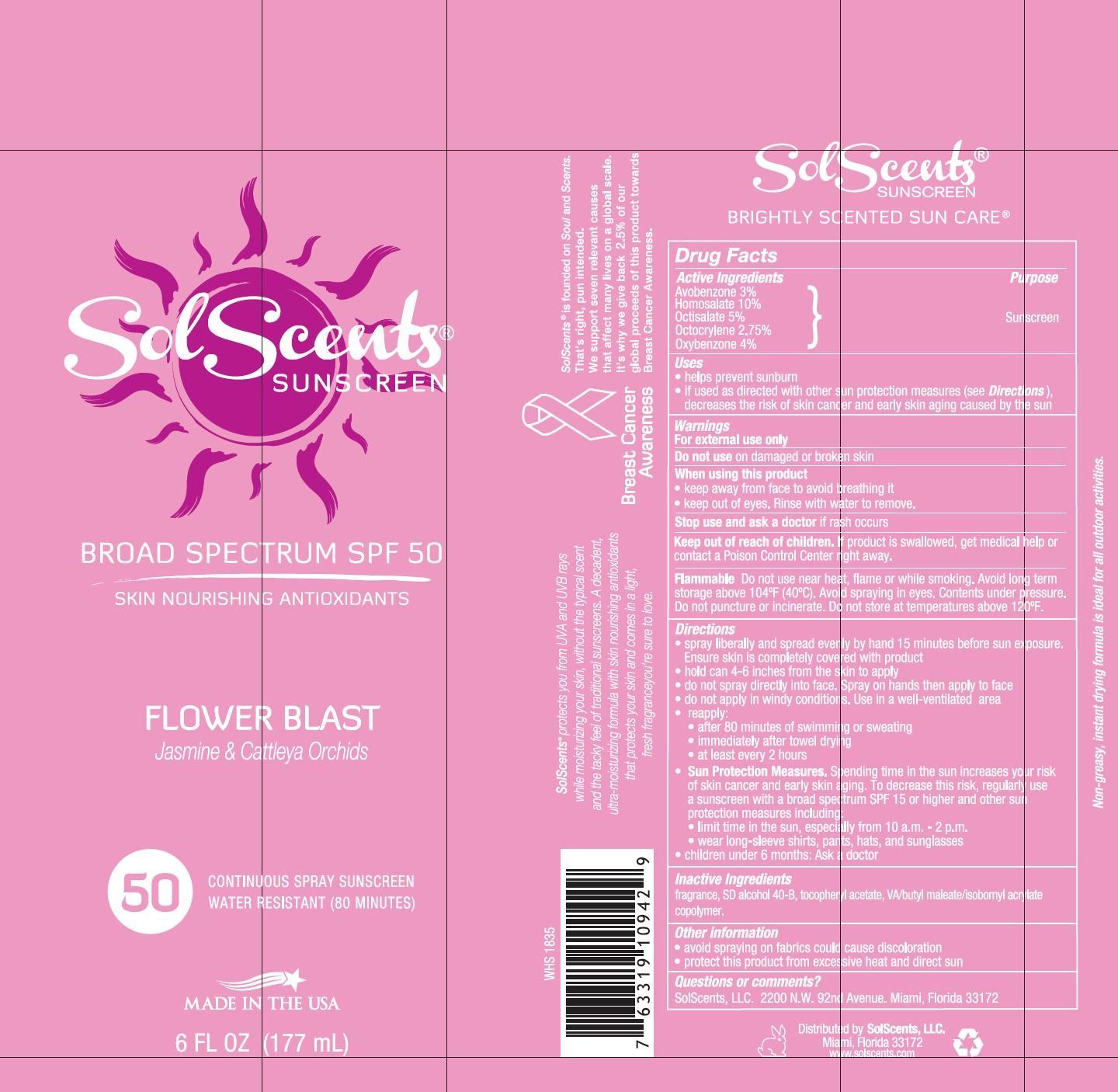 DRUG LABEL: SolScents
NDC: 13630-0076 | Form: AEROSOL, SPRAY
Manufacturer: Prime Packaging, Inc.
Category: otc | Type: HUMAN OTC DRUG LABEL
Date: 20200117

ACTIVE INGREDIENTS: AVOBENZONE 25.8 mg/1 mL; HOMOSALATE 86 mg/1 mL; OCTISALATE 43 mg/1 mL; OCTOCRYLENE 23.65 mg/1 mL; OXYBENZONE 34.4 mg/1 mL
INACTIVE INGREDIENTS: ALCOHOL; BUTYL MALEURATE; .ALPHA.-TOCOPHEROL ACETATE; ISOBORNYL ACRYLATE

Active ingredients

Avobenzone 3 %, Homosalate 10%, Octisalate 5 %, Octocrylene 2.75 %, and Oxybenzone 4 %

Purpose

Sunscreen

Uses

- helps prevent sunburn
- If use as directed with other sun protection measures (see Directions), decreases the risk of skin cancer and early skin aging caused by the sun

Warnings

OTHER SAFETY INFORMATION

For external use only

Do not use on damaged or broken skin

When using this product

- keep away from face to avoid breathing it
- keep out of eyes. Rinse with water to remove.

Stop use and ask a doctor if rash occurs

Keep out of reach of children. If product is swallowed, get medical help or contact a Poison Control Center right away.

OTHER SAFETY INFORMATION

Flammable: Do not use near heat, flame or while smoking. Avoid long term storage above 104ºF (40º). Avoid Spraying in eyes. Contents under pressure. Do not puncture or incinerate. Do not store at temperatures above 120ºF.

Directions

- spray liberally and spread evenly by hand 15 minutes before sun exposure. Ensure skin is completely covered with product
- hold container 4-6 inches from the skin to apply
- do not spray directly into face. Spray on hands then apply to face.
- do not apply in windy conditions. Use in a well-ventilated area
- reapply:
- After 80 minutes of swimming or sweating
- immediately after towel drying
- at least every 2 hours
- Sun Protection Measures. Spending time in the sun increases your risk of skin aging. To decrease this risk, regularly use a sunscreen with a broad spectrum SPF 15 or higher and othe sun protection measures including:
- limit time in the sun, especially from 10 a.m - 2 p.m.
- wear long-sleeve shirts, pants, hats, and sunglasses
- children under 6 months: Ask a doctor

Inactive Ingredients

Fragrance (Parfum), SD Alcohol 40-B (Alcohol Denat.), tocopheryl acetate, VA/Butyl Maleate/Isobornyl Acrylate Copolymer

Other Information

- avoid spraying on fabrics could cause discoloration
- protect this product from exessive heat and direct sun

Questions or comments?

SolScents, LLC.2200 N.W. 92nd Avenue. Miami, Florida 33172

PRINCIPAL DISPLAY PANEL - 177 mL Can Label

SolScents

Sunscreen

Broad spectrum SPF 50

Skin Nourishing Antioxidants

Flower Blast

Jasmine & Cattleya Orchids

50

Continuous Spray Sunscreen

Water Resistant (80 Minutes)

MADE IN THE USA

6 FL OZ (177 mL)